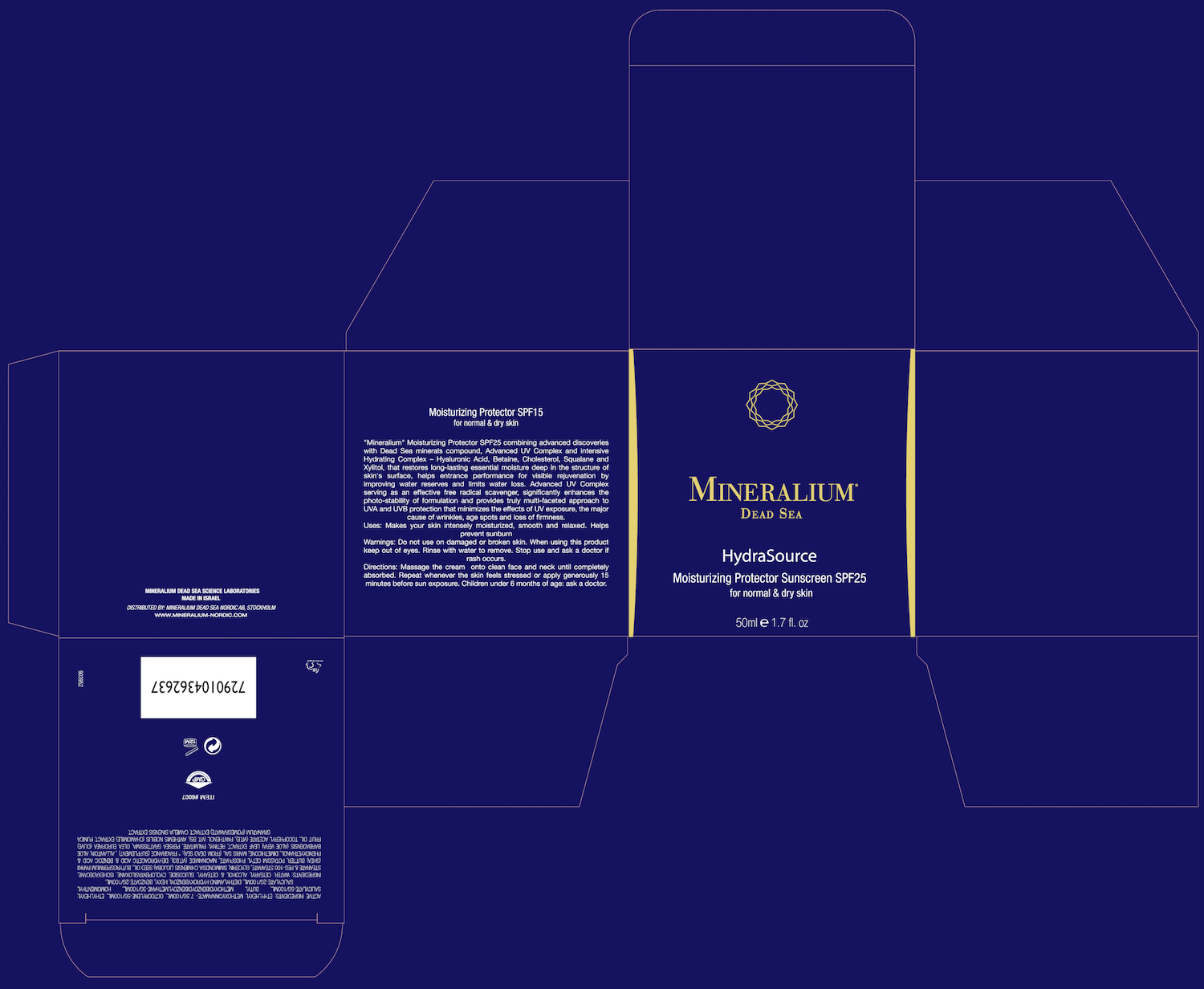 DRUG LABEL: Mineralium Hdra Source Moisturizing Protector SPF 25
NDC: 69435-1606 | Form: CREAM
Manufacturer: Peer Pharm Ltd.
Category: otc | Type: HUMAN OTC DRUG LABEL
Date: 20160325

ACTIVE INGREDIENTS: OCTOCRYLENE 5 g/100 mL; OCTINOXATE 7.5 g/100 mL; OCTISALATE 5 g/100 mL; AVOBENZONE 3 g/100 mL; HOMOSALATE 2 g/100 mL
INACTIVE INGREDIENTS: WATER; CETOSTEARYL ALCOHOL; CETEARYL GLUCOSIDE; CYCLOMETHICONE 5; ISOHEXADECANE; GLYCERIN; SIMMONDSIA CHINENSIS SEED; SHEA BUTTER; POTASSIUM CETYL PHOSPHATE; NIACINAMIDE; DIMETHICONE; SEA SALT; ALOE VERA LEAF; VITAMIN A PALMITATE; .ALPHA.-TOCOPHEROL ACETATE; PANTHENOL; CHAMOMILE FLOWER OIL; POMEGRANATE SEED OIL; CAMELINA SATIVA WHOLE

Mineralium Hdra Source Moisturizing Protector SPF 25